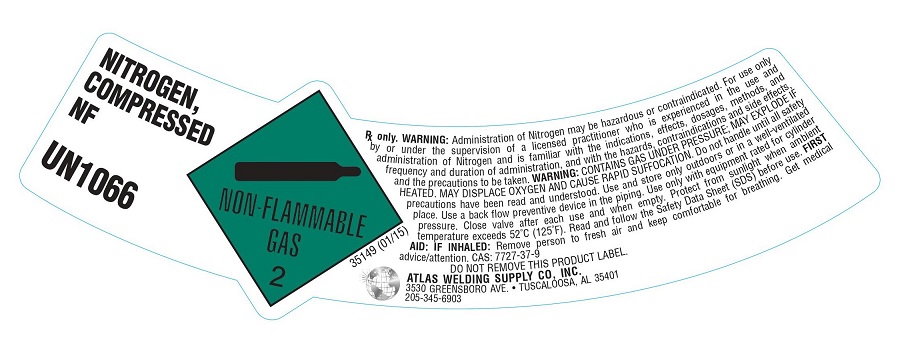 DRUG LABEL: Nitrogen
NDC: 51051-002 | Form: GAS
Manufacturer: Atlas Welding Supply Company, Inc.
Category: prescription | Type: HUMAN PRESCRIPTION DRUG LABEL
Date: 20251223

ACTIVE INGREDIENTS: NITROGEN 990 mL/1 L

Nitrogen

PACKAGE LABEL

NITROGEN, COMPRESSED NF UN1066
NON-FLAMMABLE GAS 2 NITROGEN NF
Rx only. WARNING: Administration of Nitrogen may be hazardous or contraindicated. For use only by or under the supervision of a licensed practitioner who is experienced in the use and administration of Nitrogen and is familiar with the indications, effects, dosages, methods, and frequency and duration of administration, and with the hazards, contraindications, and side effects and the precautions to be taken. WARNING: CONTAINS GAS UNDER PRESSURE; MAY EXPLODE IF HEATED. MAY DISPLACE OXYGEN AND CAUSE RAPID SUFFOCATION. Do not handle until all safety precautions have been read and understood. Use and store only outdoors or in a well-ventilated place. Use a back flow preventive device in the piping. Use only with equipment rated for cylinder pressure. Close valve after each use and when empty. Protect from sunlight when ambient temperature exceeds 52 degrees C (125 degrees F). Read and follow the Safety Data Sheet (SDS) before use. FIRST AID: IF INHALED: Remove person to fresh air and keep comfortable for breathing. Get medical advice/attention.
CAS: 7727-37-9 DO NOT REMOVE THIS PRODUCT LABEL.
ATLAS WELDING SUPPLY CO, INC. 3530 GREENSBORO AVE. . TUSCALOOSA, AL 35401 205-345-6903